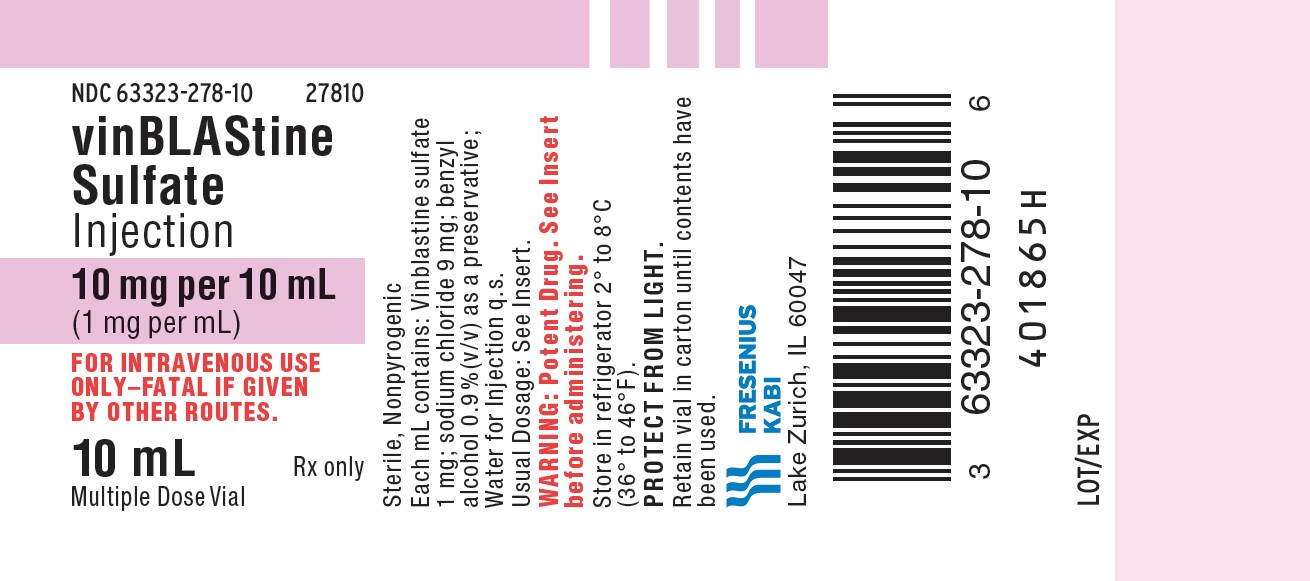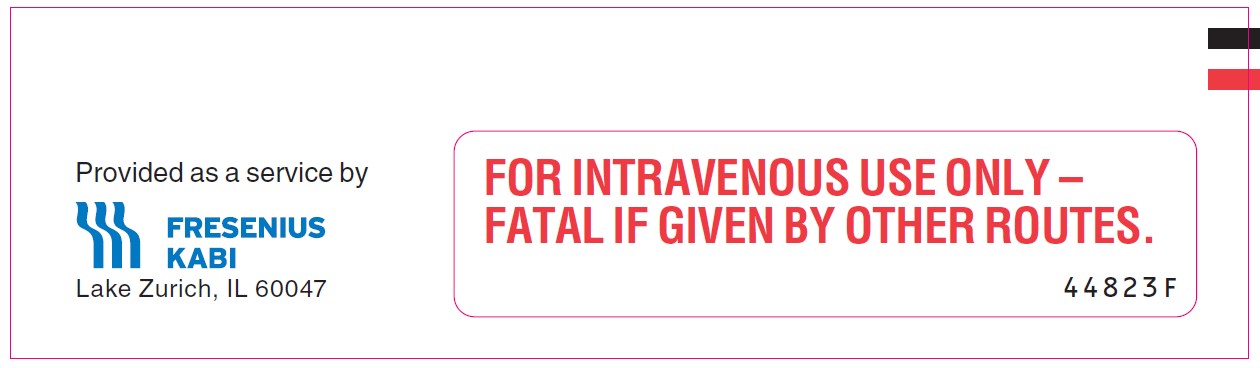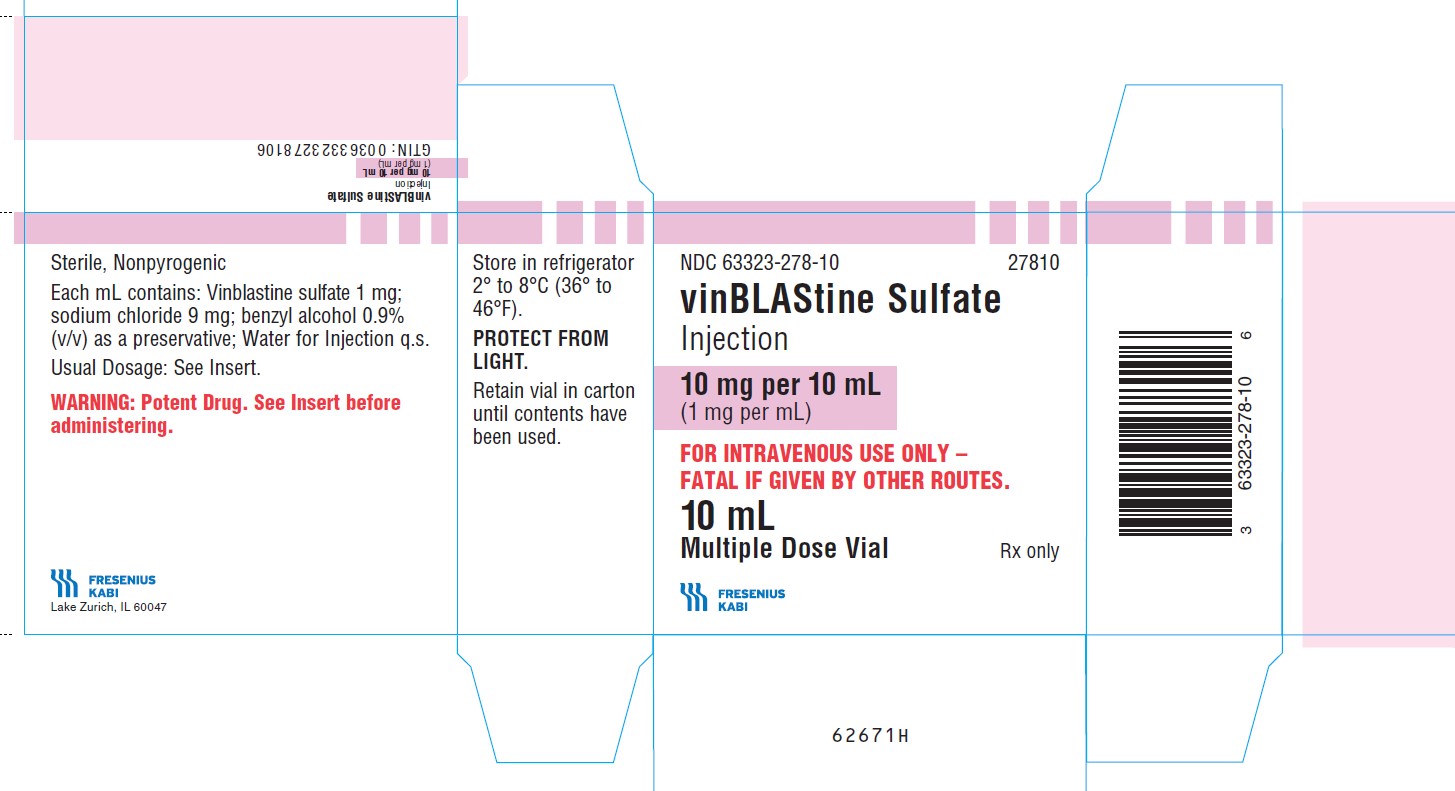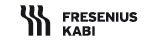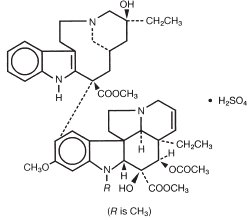 DRUG LABEL: Vinblastine Sulfate
NDC: 63323-278 | Form: INJECTION
Manufacturer: Fresenius Kabi USA, LLC
Category: prescription | Type: HUMAN PRESCRIPTION DRUG LABEL
Date: 20250415

ACTIVE INGREDIENTS: VINBLASTINE SULFATE 1 mg/1 mL
INACTIVE INGREDIENTS: SODIUM CHLORIDE 9 mg/1 mL; BENZYL ALCOHOL; WATER

vinBLAStine Sulfate

Injection

Rx only

WARNINGS

Caution: This preparation should be administered by individuals experienced in the administration of vinblastine sulfate. It is extremely important that the intravenous needle or catheter be properly positioned before any vinblastine sulfate is injected. Leakage into surrounding tissue during intravenous administration of vinblastine sulfate may cause considerable irritation. If extravasation occurs, the injection should be discontinued immediately, and any remaining portion of the dose should then be introduced into another vein. Local injection of hyaluronidase and the application of moderate heat to the area of leakage help disperse the drug and are thought to minimize discomfort and the possibility of cellulitis.

FOR INTRAVENOUS USE ONLY – FATAL IF GIVEN BY OTHER ROUTES.

See WARNINGS for the treatment of patients given intrathecal vinblastine sulfate injection.

DESCRIPTION:

Vinblastine sulfate is the salt of an alkaloid extracted from Vinca rosea Linn., a common flowering herb known as the periwinkle (more properly known as Catharanthus roseus G. Don). Previously, the generic name was vincaleukoblastine, abbreviated VLB. It is a stathmokinetic oncolytic agent. When treated in vitro with this preparation, growing cells are arrested in metaphase.

Chemical and physical evidence indicate that vinblastine sulfate is a dimeric alkaloid containing both indole and dihydroindole moieties. The accompanying structural formula has been proposed.

C46H58N4O9•H2SO4 M.W. 909.06

Each mL contains: Vinblastine sulfate 1 mg; sodium chloride 9 mg; benzyl alcohol 0.9% (v/v) as a preservative; water for injection, q.s. (pH 3.5 to 5.0).

CLINICAL PHARMACOLOGY:

Experimental data indicate that the action of vinblastine sulfate is different from that of other recognized antineoplastic agents. Tissue-culture studies suggest an interference with metabolic pathways of amino acids leading from glutamic acid to the citric acid cycle and to urea. In vivo experiments tend to confirm the in vitro results. A number of studies in vitro and in vivo have demonstrated that vinblastine sulfate produces a stathmokinetic effect and various atypical mitotic figures. The therapeutic responses, however, are not fully explained by the cytologic changes, since these changes are sometimes observed clinically and experimentally in the absence of any oncolytic effects.

Reversal of the antitumor effect of vinblastine sulfate by glutamic acid or tryptophan has been observed. In addition, glutamic acid and aspartic acid have protected mice from lethal doses of vinblastine sulfate. Aspartic acid was relatively ineffective in reversing the antitumor effect.

Other studies indicate that vinblastine sulfate has an effect on cell-energy production required for mitosis and interferes with nucleic acid synthesis. The mechanism of action of vinblastine has been related to the inhibition of microtubule formation in the mitotic spindle, resulting in an arrest of dividing cells at the metaphase stage.

Pharmacokinetic studies in patients with cancer have shown a triphasic serum decay pattern following rapid intravenous injection. The initial, middle and terminal half-lives are 3.7 minutes, 1.6 hours and 24.8 hours, respectively. The volume of the central compartment is 70% of body weight, probably reflecting very rapid tissue binding to formed elements of the blood. Extensive reversible tissue binding occurs. Low body stores are present at 48 and 72 hours after injection. Since the major route of excretion may be through the biliary system, toxicity from this drug may be increased when there is hepatic excretory insufficiency. The metabolism of vinca alkaloids has been shown to be mediated by hepatic cytochrome P450 isoenzymes in the CYP 3A subfamily. This metabolic pathway may be impaired in patients with hepatic dysfunction or who are taking concomitant potent inhibitors of these isoenzymes such as erythromycin. Enhanced toxicity has been reported in patients receiving concomitant erythromycin (see PRECAUTIONS). Following injection of tritiated vinblastine in the human cancer patient, 10% of the radioactivity was found in the feces and 14% in the urine; the remaining activity was not accounted for. Similar studies in dogs demonstrated that, over nine days, 30 to 36% of radioactivity was found in the bile and 12 to 17% in the urine. A similar study in the rat demonstrated that the highest concentrations of radioactivity were found in the lung, liver, spleen and kidney two hours after injection.

Hematologic Effects

Clinically, leukopenia is an expected effect of vinblastine sulfate, and the level of the leukocyte count is an important guide to therapy with this drug. In general, the larger the dose employed, the more profound and longer lasting the leukopenia will be. The fact that the white blood cell count returns to normal levels after drug-induced leukopenia is an indication that the white cell-producing mechanism is not permanently depressed. Usually, the white count has completely returned to normal after the virtual disappearance of white cells from the peripheral blood.

Following therapy with vinblastine sulfate, the nadir in white blood cell count may be expected to occur five to ten days after the last day of drug administration. Recovery of the white blood count is fairly rapid thereafter and is usually complete within another 7 to 14 days. With the smaller doses employed for maintenance therapy, leukopenia may not be a problem.

Although the thrombocyte count ordinarily is not significantly lowered by therapy with vinblastine sulfate, patients whose bone marrow has been recently impaired by prior therapy with radiation or with other oncolytic drugs may show thrombocytopenia (less than 200,000 platelets/mm^3). When other chemotherapy or radiation has not been employed previously, thrombocyte reduction below the level of 200,000/mm^3 is rarely encountered, even when vinblastine sulfate may be causing significant leukopenia. Rapid recovery from thrombocytopenia within a few days is the rule.

The effect of vinblastine sulfate upon the red cell count and hemoglobin is usually insignificant when other therapy does not complicate the picture. It should be remembered, however, that patients with malignant disease may exhibit anemia even in the absence of any therapy.

INDICATIONS AND USAGE:

Vinblastine Sulfate Injection is indicated in the palliative treatment of the following:

I. Frequently Responsive Malignancies

- Generalized Hodgkin’s disease (Stages III and IV, Ann Arbor modification of Rye staging system)
- Lymphocytic lymphoma (nodular and diffuse, poorly and well differentiated)
- Histiocytic lymphoma
- Mycosis fungoides (advanced stages)
- Advanced carcinoma of the testis
- Kaposi’s sarcoma
- Letterer-Siwe disease (histiocytosis X)

II. Less Frequently Responsive Malignancies

- Choriocarcinoma resistant to other chemotherapeutic agents
- Carcinoma of the breast, unresponsive to appropriate endocrine surgery and hormonal therapy
  Current principles of chemotherapy for many types of cancer include the concurrent administration of several antineoplastic agents. For enhanced therapeutic effect without additive toxicity, agents with different dose-limiting clinical toxicities and different mechanisms of action are generally selected. Therefore, although vinblastine sulfate is effective as a single agent in the aforementioned indications, it is usually administered in combination with other antineoplastic drugs. Such combination therapy produces a greater percentage of response than does a single-agent regimen. These principles have been applied, for example, in the chemotherapy of Hodgkin’s disease.

Hodgkin's Disease

Vinblastine sulfate has been shown to be one of the most effective single agents for the treatment of Hodgkin’s disease. Advanced Hodgkin’s disease has also been successfully treated with several multiple-drug regimens that included vinblastine sulfate. Patients who had relapses after treatment with the MOPP program - mechlorethamine hydrochloride (nitrogen mustard), vincristine sulfate, prednisone and procarbazine - have likewise responded to combination-drug therapy that included vinblastine sulfate. A protocol using cyclophosphamide in place of nitrogen mustard and vinblastine sulfate instead of vincristine sulfate is an alternative therapy for previously untreated patients with advanced Hodgkin’s disease.

Advanced testicular germinal-cell cancers (embryonal carcinoma, teratocarcinoma and choriocarcinoma) are sensitive to vinblastine sulfate alone, but better clinical results are achieved when vinblastine sulfate is administered concomitantly with other antineoplastic agents. The effect of bleomycin is significantly enhanced if vinblastine sulfate is administered six to eight hours prior to the administration of bleomycin; this schedule permits more cells to be arrested during metaphase, the stage of the cell cycle in which bleomycin is active.

CONTRAINDICATIONS:

Vinblastine sulfate is contraindicated in patients who have significant granulocytopenia unless this is a result of the disease being treated. It should not be used in the presence of bacterial infections. Such infections must be brought under control prior to the initiation of therapy with vinblastine sulfate.

WARNINGS:

This preparation is for intravenous use only. It should be administered by individuals experienced in the administration of vinblastine sulfate. The intrathecal administration of vinblastine sulfate usually results in death.

To reduce the potential for fatal medication errors due to incorrect route of administration, vinblastine sulfate injection should be diluted in a flexible plastic container and prominently labeled (as indicated) “FOR INTRAVENOUS USE ONLY – FATAL IF GIVEN BY OTHER ROUTES.’’

After inadvertent intrathecal administration of vinca alkaloids, immediate neurosurgical intervention is required in order to prevent ascending paralysis leading to death. In a very small number of patients, life-threatening paralysis and subsequent death was averted but resulted in devastating neurological sequelae, with limited recovery afterwards.

There are no published cases of survival following intrathecal administration of vinblastine sulfate to base treatment on. However, based on the published management of survival cases involving the related vinca alkaloid vincristine sulfate^1-3, if vinblastine sulfate is mistakenly given by the intrathecal route, the following treatment should be initiated immediately after the injection:

1. Removal of as much CSF as is safely possible through the lumbar access.

2. Insertion of an epidural catheter into the subarachnoid space via the intervertebral space above initial lumbar access and CSF irrigation with lactated Ringer’s solution. Fresh frozen plasma should be requested and, when available, 25 mL should be added to every 1 liter of lactated Ringer’s solution.

3. Insertion of an intraventricular drain or catheter by a neurosurgeon and continuation of CSF irrigation with fluid removal through the lumbar access connected to a closed drainage system. Lactated Ringer’s solution should be given by continuous infusion at 150 mL/hour, or at a rate of 75 mL/hour when fresh frozen plasma has been added as above.

The rate of infusion should be adjusted to maintain a spinal fluid protein level of 150 mg/dL.

The following measures have also been used in addition but may not be essential:

Glutamic acid, 10 grams, has been given intravenously over 24 hours, followed by 500 mg three times daily by mouth for 1 month. Folinic acid has been administered intravenously as a 100 mg bolus and then infused at a rate of 25 mg/hour for 24 hours, then bolus doses of 25 mg every 6 hours for 1 week. Pyridoxine has been given at a dose of 50 mg every 8 hours by intravenous infusion over 30 minutes. Their roles in the reduction of neurotoxicity are unclear.

Pregnancy Category D

Caution is necessary with the administration of all oncolytic drugs during pregnancy. Information on the use of vinblastine sulfate during human pregnancy is very limited. Animal studies with vinblastine sulfate suggest that teratogenic effects may occur. Vinblastine sulfate can cause fetal harm when administered to a pregnant woman. Laboratory animals given this drug early in pregnancy suffer resorption of the conceptus; surviving fetuses demonstrate gross deformities. There are no adequate and well-controlled studies in pregnant women. If this drug is used during pregnancy, or if the patient becomes pregnant while receiving this drug, she should be apprised of the potential hazard to the fetus. Women of childbearing potential should be advised to avoid becoming pregnant.

Aspermia has been reported in man. Animal studies show metaphase arrest and degenerative changes in germ cells.

Leukopenia (granulocytopenia) may reach dangerously low levels following administration of the higher recommended doses. It is therefore important to follow the dosage technique recommended under DOSAGE AND ADMINISTRATION. Stomatitis and neurologic toxicity, although not common or permanent, can be disabling.

PRECAUTIONS:

General

Toxicity may be enhanced in the presence of hepatic insufficiency.

If leukopenia with less than 2,000 white blood cells/mm^3 occurs following a dose of vinblastine sulfate, the patient should be watched carefully for evidence of infection until the white blood cell count has returned to a safe level.

When cachexia or ulcerated areas of the skin surface are present, there may be a more profound leukopenic response to the drug; therefore, its use should be avoided in older persons suffering from either of these conditions.

In patients with malignant-cell infiltration of the bone marrow, the leukocyte and platelet counts have sometimes fallen precipitously after moderate doses of vinblastine sulfate. Further use of the drug in such patients is inadvisable.

Acute shortness of breath and severe bronchospasm have been reported following the administration of vinca alkaloids. These reactions have been encountered most frequently when the vinca alkaloid was used in combination with mitomycin-C and may require aggressive treatment, particularly when there is pre-existing pulmonary dysfunction. The onset may be within minutes or several hours after the vinca is injected and may occur up to two weeks following a dose of mitomycin. Progressive dyspnea requiring chronic therapy may occur. Vinblastine should not be readministered.

Care should be recommended in patients with ischemic cardiac disease.

The use of small amounts of vinblastine sulfate daily for long periods is not advised, even though the resulting total weekly dosage may be similar to that recommended. Little or no added therapeutic effect has been demonstrated when such regimens have been used. Strict adherence to the recommended dosage schedule is very important. When amounts equal to several times the recommended weekly dosage were given in seven daily installments for long periods, convulsions, severe and permanent central nervous system damage, and even death occurred.

Care must be taken to avoid contamination of the eye with concentrations of vinblastine sulfate used clinically. If accidental contamination occurs, severe irritation (or, if the drug was delivered under pressure, even corneal ulceration) may result. The eye should be washed with water immediately and thoroughly.

Information for Patients

The patient should be warned to report immediately the appearance of sore throat, fever, chills or sore mouth. Advice should be given to avoid constipation, and the patient should be made aware that alopecia may occur and that jaw pain and pain in the organs containing tumor tissue may occur. The latter is thought possibly to result from swelling of tumor tissue during its response to treatment. Scalp hair will regrow to its pretreatment extent even with continued treatment with vinblastine sulfate. Nausea and vomiting, although not common, may occur. Any other serious medical event should be reported to the physician.

Laboratory Tests

Since dose-limiting clinical toxicity is the result of depression of the white blood cell count, it is imperative that this count be obtained just before the planned dose of vinblastine sulfate. Following administration of vinblastine sulfate, a fall in the white blood cell count may occur. The nadir of this fall is observed from 5 to 10 days following a dose. Recovery to pretreatment levels is usually observed from 7 to 14 days after treatment. These effects will be exaggerated when pre-existing bone marrow damage is present and also with the higher recommended doses (see DOSAGE AND ADMINISTRATION). The presence of this drug or its metabolites in blood or body tissues is not known to interfere with clinical laboratory tests.

Drug Interactions

The simultaneous oral or intravenous administration of phenytoin and antineoplastic chemotherapy combinations that included vinblastine sulfate has been reported to have reduced blood levels of the anticonvulsant and to have increased seizure activity. Dosage adjustment should be based on serial blood level monitoring. The contribution of vinblastine sulfate to this interaction is not certain. The interaction may result from either reduced absorption of phenytoin or an increase in the rate of its metabolism and elimination.

Caution should be exercised in patients concurrently taking drugs known to inhibit drug metabolism by hepatic cytochrome P450 isoenzymes in the CYP 3A subfamily, or in patients with hepatic dysfunction. Concurrent administration of vinblastine sulfate with an inhibitor of this metabolic pathway may cause an earlier onset and/or an increased severity of side effects. Enhanced toxicity has been reported in patients receiving concomitant erythromycin (see ADVERSE REACTIONS).

Carcinogenesis, Mutagenesis, Impairment of Fertility

Aspermia has been reported in man. Animal studies suggest that teratogenic effects may occur. See WARNINGS regarding impaired fertility. Animal studies have shown metaphase arrest and degenerative changes in germ cells. Amenorrhea has occurred in some patients treated with the combination consisting of an alkylating agent, procarbazine, prednisone and vinblastine sulfate. Its occurrence was related to the total dose of these four agents used. Recovery of menses was frequent. The same combination of drugs given to male patients produced azoospermia; if spermatogenesis did return, it was not likely to do so with less than two years of unmaintained remission.

Mutagenicity - Tests in Salmonella typhimurium and with the dominant lethal assay in mice failed to demonstrate mutagenicity. Sperm abnormalities have been noted in mice. Vinblastine sulfate has produced an increase in micronuclei formation in bone marrow cells of mice; however, since vinblastine sulfate inhibits mitotic spindle formation, it cannot be concluded that this is evidence of mutagenicity. Additional studies in mice demonstrated no reduction in fertility of males. Chromosomal translocations did occur in male mice. First-generation male offspring of these mice were not heterozygous translocation carriers.

In vitro tests using hamster lung cells in culture have produced chromosomal changes, including chromatid breaks and exchanges, whereas tests using another type of hamster cell failed to demonstrate mutation. Breaks and aberrations were not observed on chromosome analysis of marrow cells from patients being treated with this drug.

It is not clear from the literature how this drug affects synthesis of DNA and RNA. Some believe that there is no interference. Others believe that vinblastine interferes with nucleic acid metabolism but may not do so by direct effect but possibly as the result of biochemical disturbance in some other part of the molecular organization of the cell. No inhibition of RNA synthesis occurred in rat hepatoma cells exposed in culture to noncytotoxic levels of vinblastine. Conflicting results have been noted by others regarding interference with DNA synthesis.

Carcinogenesis - There is no currently available evidence to indicate that vinblastine sulfate itself has been carcinogenic in humans since the inception of its clinical use in the late 1950’s. Patients treated for Hodgkin’s disease have developed leukemia following radiation therapy and administration of vinblastine sulfate in combination with other chemotherapy including agents known to intercalate with DNA. It is not known to what extent vinblastine sulfate may have contributed to the appearance of leukemia. Available data in rats and mice have failed to demonstrate clearly evidence of carcinogenesis when the animals were treated with the maximum tolerated dose and with one-half that dose for six months. This testing system demonstrated that other agents were clearly carcinogenic, whereas vinblastine sulfate was in the group of drugs causing slightly increased or the same tumor incidence as controls in one study and 1.5 to two-fold increase in tumor incidence over controls in another study.

Usage in Pregnancy

Pregnancy Category D - (See WARNINGS). Vinblastine sulfate should be given to a pregnant woman only if clearly needed. Animal studies suggest that teratogenic effects may occur.

Pediatric Use

The dosage schedule for pediatric patients is indicated under DOSAGE AND ADMINISTRATION.

Nursing Mothers

It is not known whether this drug is excreted in human milk. Because many drugs are excreted in human milk and because of the potential for serious adverse reactions from vinblastine sulfate in nursing infants, a decision should be made whether to discontinue nursing or the drug, taking into account the importance of the drug to the mother.

ADVERSE REACTIONS:

Prior to the use of the drug, patients should be advised of the possibility of untoward symptoms.

In general, the incidence of adverse reactions attending the use of vinblastine sulfate appears to be related to the size of the dose employed. With the exception of epilation, leukopenia and neurologic side effects, adverse reactions generally have not persisted for longer than 24 hours. Neurologic side effects are not common; but when they do occur, they often last for more than 24 hours. Leukopenia, the most common adverse reaction, is usually the dose-limiting factor.

The following are manifestations that have been reported as adverse reactions, in decreasing order of frequency. The most common adverse reactions are underlined:

Hematologic - Leukopenia (granulocytopenia), anemia, thrombocytopenia (myelosuppression).

Dermatologic - Alopecia is common. A single case of light sensitivity associated with this product has been reported.

Gastrointestinal - Constipation, anorexia, nausea, vomiting, abdominal pain, ileus, vesiculation of the mouth, pharyngitis, diarrhea, hemorrhagic enterocolitis, bleeding from an old peptic ulcer and rectal bleeding.

Neurologic - Numbness of digits (paresthesias), loss of deep tendon reflexes, peripheral neuritis, mental depression, headache, convulsions.

Treatment with vinca alkaloids has resulted rarely in both vestibular and auditory damage to the eighth cranial nerve. Manifestations include partial or total deafness which may be temporary or permanent, and difficulties with balance including dizziness, nystagmus and vertigo. Particular caution is warranted when vinblastine sulfate is used in combination with other agents known to be ototoxic such as the platinum-containing oncolytics.

Cardiovascular - Hypertension—Cardiac effects such as myocardial infarction, angina pectoris and transient abnormalities of ECG related to coronary ischemia have been reported very rarely. Cases of unexpected myocardial infarction and cerebrovascular accidents have occurred in patients undergoing combination chemotherapy with vinblastine, bleomycin and cisplatin. Raynaud’s phenomenon has also been reported with this combination.

Pulmonary - See PRECAUTIONS.

Miscellaneous - Malaise, bone pain, weakness, pain in tumor-containing tissue, dizziness, jaw pain, skin vesiculation, hypertension, Raynaud’s phenomenon when patients are being treated with vinblastine sulfate in combination with bleomycin and cis-platinum for testicular cancer. The syndrome of inappropriate secretion of antidiuretic hormone has occurred with higher than recommended doses.

Nausea and vomiting usually may be controlled with ease by antiemetic agents. When epilation develops, it frequently is not total; and, in some cases, hair regrows while maintenance therapy continues.

Extravasation during intravenous injection may lead to cellulitis and phlebitis. If the amount of extravasation is great, sloughing may occur.

OVERDOSAGE:

Signs and Symptoms

Side effects following the use of vinblastine sulfate are dose related. Therefore, following administration of more than the recommended dose, patients can be expected to experience these effects in an exaggerated fashion. (See CLINICAL PHARMACOLOGY, CONTRAINDICATIONS, WARNINGS, PRECAUTIONS and ADVERSE REACTIONS.) There is no specific antidote. In addition, neurotoxicity similar to that with vincristine sulfate may be observed. Since the major route of excretion may be through the biliary system, toxicity from this drug may be increased when there is hepatic insufficiency.

Treatment

To obtain up-to-date information about the treatment of overdose, a good resource is your certified Regional Poison Control Center. Telephone numbers of certified poison control centers are listed in the Physicians’ Desk Reference (PDR). In managing overdosage, consider the possibility of multiple drug overdoses, interaction among drugs and unusual drug kinetics in your patient. Overdoses of vinblastine sulfate have been reported rarely. The following is provided to serve as a guide should such an overdose be encountered.

Supportive care should include the following: (1) prevention of side effects that result from the syndrome of inappropriate secretion of antidiuretic hormone (this would include restriction of the volume of daily fluid intake to that of the urine output plus insensible loss and perhaps the administration of a diuretic affecting the function of the loop of Henle and the distal tubule); (2) administration of an anticonvulsant; (3) prevention of ileus: (4) monitoring the cardiovascular system; and (5) determining daily blood counts for guidance in transfusion requirements and assessing the risk of infection. The major effect of excessive doses of vinblastine sulfate will be myelosuppression, which may be life-threatening. There is no information regarding the effectiveness of dialysis nor of cholestyramine for the treatment of overdosage.

Vinblastine sulfate in the dry state is irregularly and unpredictably absorbed from the gastrointestinal tract following oral administration. Absorption of the solution has not been studied. If vinblastine is swallowed, activated charcoal in a water slurry may be given by mouth along with a cathartic. The use of cholestyramine in this situation has not been reported.

Symptoms of overdose will appear when greater-than-recommended doses are given. Any dose of vinblastine sulfate that results in elimination of platelets and neutrophils from blood and marrow and their precursors from marrow should be considered life-threatening. The exact dose that will do this in all patients is unknown. Overdoses occurring during prolonged consecutive-day infusions may be more toxic than the same total dose given by rapid intravenous injection. The intravenous median lethal dose in mice is 10 mg/kg body weight; in rats, it is 2.9 mg/kg. The oral median lethal dose in rats is 7 mg/kg.

Protect the patient’s airway and support ventilation and perfusion. Meticulously monitor and maintain, within acceptable limits, the patient’s vital signs, blood gases, serum electrolytes, etc. Absorption of drugs from the gastrointestinal tract may be decreased by giving activated charcoal, which, in many cases, is more effective than emesis or lavage; consider charcoal instead of or in addition to gastric emptying if the drug has been swallowed. Repeated doses of charcoal over time may hasten elimination of some drugs that have been absorbed. Safeguard the patient’s airway when employing gastric emptying or charcoal.

DOSAGE AND ADMINISTRATION:

This preparation is for intravenous use only (see WARNINGS).

Special Dispensing Information- To reduce the potential for fatal medication errors due to incorrect route of administration, vinblastine sulfate injection should be diluted in a flexible plastic container and prominently labeled (as indicated), “FOR INTRAVENOUS USE ONLY – FATAL IF GIVEN BY OTHER ROUTES.” (see WARNINGS).

Preparation for flexible plastic container

Vinblastine sulfate injection when diluted with 0.9% sodium chloride injection to concentrations of 0.1 mg/mL to 0.4 mg/mL is stable at room temperature for up to 24 hours when protected from light or 8 hours in normal light.

Caution–It is extremely important that the intravenous needle or catheter be properly positioned before any vinblastine sulfate is injected. Leakage into surrounding tissue during intravenous administration of vinblastine sulfate may cause considerable irritation. If extravasation occurs, the injection should be discontinued immediately and any remaining portion of the dose should then be introduced into another vein. Local injection of hyaluronidase and the application of moderate heat to the area of leakage will help disperse the drug and may minimize discomfort and the possibility of cellulitis.

There are variations in the depth of the leukopenic response that follows therapy with vinblastine sulfate. For this reason, it is recommended that the drug be given no more frequently than once every seven days.

Adult Patients

It is wise to initiate therapy for adults by administering a single intravenous dose of 3.7 mg/m^2 of body surface area (bsa). Thereafter, white blood cell counts should be made to determine the patient’s sensitivity to vinblastine sulfate.

A simplified and conservative incremental approach to dosage at weekly intervals for adults may be outlined as follows:

First dose ....................................... 3.7 mg/m^2 bsa
Second dose .................................. 5.5 mg/m^2 bsa
Third dose ...................................... 7.4 mg/m^2 bsa
Fourth dose .................................. 9.25 mg/m^2 bsa
Fifth dose ..................................... 11.1 mg/m^2 bsa

The above-mentioned increases may be used until a maximum dose not exceeding 18.5 mg/m^2 bsa for adults is reached. The dose should not be increased after that dose which reduces the white cell count to approximately 3,000 cells/mm^3. In some adults, 3.7 mg/m^2 bsa may produce this leukopenia; other adults may require more than 11.1 mg/m^2 bsa; and, very rarely, as much as 18.5 mg/m^2 bsa may be necessary. For most adult patients, however, the weekly dosage will prove to be 5.5 to 7.4 mg/m^2 bsa.

When the dose of vinblastine sulfate which will produce the above degree of leukopenia has been established, a dose of one increment smaller than this should be administered at weekly intervals for maintenance. Thus, the patient is receiving the maximum dose that does not cause leukopenia. It should be emphasized that, even though seven days have elapsed, the next dose of vinblastine sulfate should not be given until the white cell count has returned to at least 4,000/mm^3. In some cases, oncolytic activity may be encountered before leukopenic effect. When this occurs, there is no need to increase the size of subsequent doses (see PRECAUTIONS).

Pediatric Patients

A review of published literature from 1993 to 1995 showed that initial doses of vinblastine sulfate in pediatric patients varied depending on the schedule used and whether vinblastine sulfate was administered as a single agent or incorporated within a particular chemotherapeutic regimen. As a single agent for Letterer-Siwe disease (histiocytosis X), the initial dose of vinblastine sulfate was reported as 6.5 mg/m^2. When vinblastine sulfate was used in combination with other chemotherapeutic agents for the treatment of Hodgkin’s disease, the initial dose was reported as 6 mg/m^2. For testicular germ cell carcinomas, the initial dose of vinblastine sulfate was reported as 3 mg/m^2 in a combination regimen. Dose modifications should be guided by hematologic tolerance.

Patients with Renal or Hepatic Impairment

A reduction of 50% in the dose of vinblastine sulfate is recommended for patients having a direct serum bilirubin value above 3 mg/100 mL. Since metabolism and excretion are primarily hepatic, no modification is recommended for patients with impaired renal function.

The duration of maintenance therapy varies according to the disease being treated and the combination of antineoplastic agents being used. There are differences of opinion regarding the duration of maintenance therapy with the same protocol for a particular disease; for example, various durations have been used with the MOPP program in treating Hodgkin’s disease. Prolonged chemotherapy for maintaining remissions involves several risks, among which are life-threatening infectious diseases, sterility and possibly the appearance of other cancers through suppression of immune surveillance.

In some disorders, survival following complete remission may not be as prolonged as that achieved with shorter periods of maintenance therapy. On the other hand, failure to provide maintenance therapy in some patients may lead to unnecessary relapse; complete remissions in patients with testicular cancer, unless maintained for at least two years, often result in early relapse. The calculated dose of vinblastine sulfate may be infused from a flexible plastic container directly into an intravenous catheter/needle or into a running intravenous infusion. If care is taken to ensure that the needle is securely within the vein and that no solution containing vinblastine sulfate is spilled extravascularly, cellulitis and/or phlebitis will not occur. To minimize further the possibility of extravascular spillage, flush the infusion line with normal saline prior to removal of the intravenous catheter or needle. The dose should not be diluted in large volumes of diluent (i.e. greater than 100 mL) or given intravenously for prolonged periods (longer than 30 minutes), since this frequently results in irritation of the vein and increases the chance of extravasation.

Because of the enhanced possibility of thrombosis, it is considered inadvisable to inject a solution of vinblastine sulfate into an extremity in which the circulation is impaired or potentially impaired by such conditions as compressing or invading neoplasm, phlebitis or varicosity.

Parenteral drug products should be inspected visually for particulate matter and discoloration prior to administration, whenever solution and container permit.

Procedures for proper handling and disposal of anti-cancer drugs should be considered. Several guidelines on this subject have been published.^4-10 There is no general agreement that all of the procedures recommended in the guidelines are necessary or appropriate.

HOW SUPPLIED:

Vinblastine Sulfate Injection is supplied as follows:

Product Code | NDC No. | Strength
27810 | 63323-278-10 | 10 mg per 10 mL (1 mg per mL) | 10 mL flip-top vial, individually packaged.

Store products in refrigerator 2° to 8°C (36° to 46°F) to assure extended stability.

PROTECT FROM LIGHT. Retain vial in carton until time of use.

REFERENCES:

1. Dyke. Treatment of inadvertent intrathecal injection of vincristine. N Engl J. Med, 1989; 321: 1270-71.
2. Michelagnoli MP, Bailey CC, Wilson L, Livingston J, Kinsey SB. Potential salvage therapy for inadvertent intrathecal administration of vincristine. Br. J. Haematology, 1997; 99: 364-367. (Mfr. Control No. GB97113451A).
3. Zaragoza MR, Ritchey ML, Walter A. Neurourologic consequences of accidental intrathecal vincristine: A case report. Med. Pediatr. Oncol, 1995; 24(1): 61-62.
4. Recommendations for the Safe Handling of Parenteral Antineoplastic Drugs, NIH Publication No. 83-2621. For sale by the Superintendent of Documents, U.S. Government Printing Office, Washington, DC 20402.
5. AMA Council Report. Guidelines for Handling Parenteral Antineoplastics. JAMA, 1985; 253(11): 1590-1592.
6. National Study Commission on Cytotoxic Exposure– Recommendations for Handling Cytotoxic Agents. Available from Louis P. Jeffrey, ScD., Chairman, National Study Commission on Cytotoxic Exposure, Massachusetts College of Pharmacy and Allied Health Sciences, 179 Longwood Avenue, Boston, Massachusetts 02115.
7. Clinical Oncological Society of Australia. Guidelines and Recommendations for Safe Handling of Antineoplastic Agents. Med J Australia, 1983; 1:426-428.
8. Jones RB, et al. Safe Handling of Chemotherapeutic Agents: A Report from the Mount Sinai Medical Center. CA–A Cancer Journal for Clinicians, 1983; (Sept/Oct) 258-263.
9. American Society of Hospital Pharmacists Technical Assistance Bulletin on Handling Cytotoxic and Hazardous Drugs. Am J. Hosp Pharm, 1990; 47:1033-1049.
10. OSHA Work-Practice Guidelines for Personnel Dealing with Cytotoxic (Antineoplastic) Drugs. Am J. Hosp Pharm, 1986; 43:1193-1204.

Lake Zurich, IL 60047

www.fresenius-kabi.com/us

45843H

Revised: February 2025

PACKAGE LABEL - PRINCIPAL DISPLAY – vinBLAStine Sulfate Injection 10 mL Multiple Dose Vial Label

NDC 63323-278-10 27810

vinBLAStine Sulfate Injection

10 mg per 10 mL

(1 mg per mL)

FOR INTRAVENOUS USE ONLY – FATAL IF GIVEN BY OTHER ROUTES.

10 mL Rx only

Multiple Dose Vial

PACKAGE LABEL - PRINCIPAL DISPLAY – vinBLAStine Sulfate Injection Sticker Label

FOR INTRAVENOUS USE ONLY – FATAL IF GIVEN BY OTHER ROUTES.

PACKAGE LABEL - PRINCIPAL DISPLAY – vinBLAStine Sulfate Injection 10 mL Multiple Dose Carton Label

NDC 63323-278-10 27810

vinBLAStine Sulfate Injection

10 mg per 10 mL

(1 mg per mL)

FOR INTRAVENOUS USE ONLY – FATAL IF GIVEN BY OTHER ROUTES.

10 mL

Multiple Dose Vial Rx only